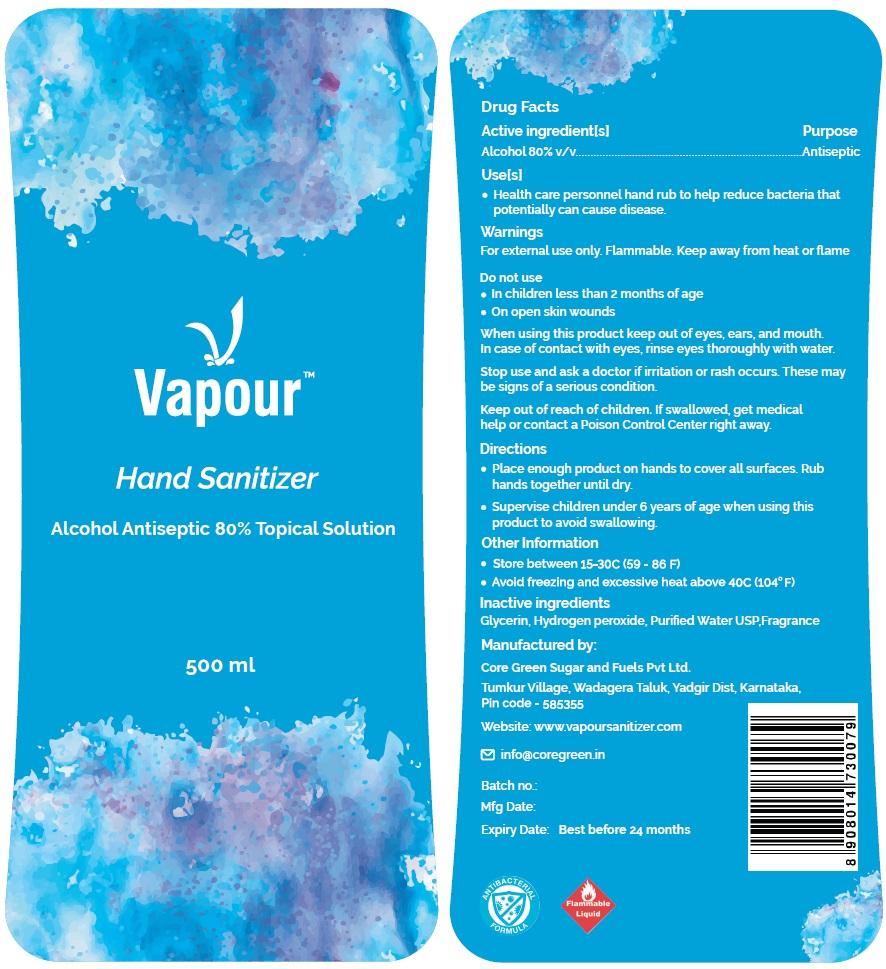 DRUG LABEL: Vapour Hand Sanitizer
NDC: 80880-100 | Form: LIQUID
Manufacturer: CORE GREEN SUGAR AND FUELS PRIVATE LIMITED
Category: otc | Type: HUMAN OTC DRUG LABEL
Date: 20201109

ACTIVE INGREDIENTS: ALCOHOL 80 mL/100 mL
INACTIVE INGREDIENTS: GLYCERIN; HYDROGEN PEROXIDE; WATER

VapourTM Hand Sanitizer

Active ingredient[s]

Alcohol 80% v/v

Purpose

Antiseptic

Use[s]

• Health care personnel hand rub to help reduce bacteria that potentially can cause disease.

Warnings

For external use only. Flammable. Keep away from heat or flame

Do not use

• In children less than 2 months of age
• On open skin wounds

When using this product keep out of eyes, ears, and mouth. In case of contact with eyes, rinse eyes thoroughly with water.

Stop use and ask a doctor if irritation or rash occurs. These may be signs of a serious condition.

Keep out of reach of children. If swallowed, get medical help or contact a Poison Control Center right away.

Directions

• Place enough product on hands to cover all surfaces. Rub hands together until dry.

• Supervise children under 6 years of age when using this product to avoid swallowing.

Other Information

• Store between 15-30C (59 - 86 F)
• Avoid freezing and excessive heat above 40C (104°F)

Inactive ingredients

Glycerin, Hydrogen peroxide, Purified Water USP,Fragrance

Alcohol Antiseptic 80% Topical Solution

Manufactured by:

Core Green Sugar and Fuels Pvt Ltd.

Tumkur Village, Wadagera Taluk, Yadgir Dist, Karnataka,

Pin code - 585355

Website: www.vapoursanitizer.com

info@coregreen.in

Expiry Date: Best before 24 months